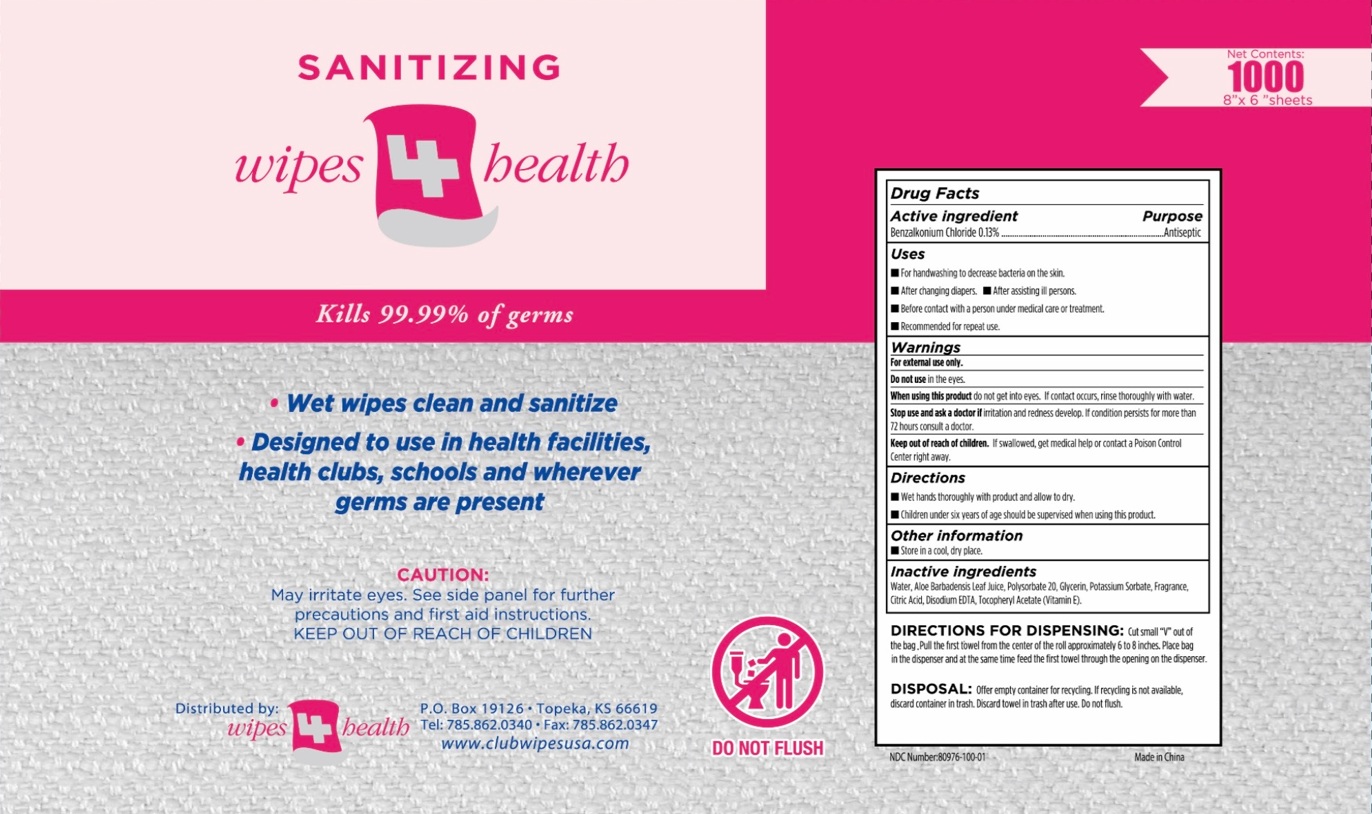 DRUG LABEL: WIPES4HEALTH
NDC: 80976-100 | Form: CLOTH
Manufacturer: Bubble Marketing LLC
Category: otc | Type: HUMAN OTC DRUG LABEL
Date: 20260203

ACTIVE INGREDIENTS: BENZALKONIUM CHLORIDE 0.13 g/100 mL
INACTIVE INGREDIENTS: WATER; ALOE VERA LEAF JUICE; POLYSORBATE 20; GLYCERIN; POTASSIUM SORBATE; CITRIC ACID MONOHYDRATE; EDETATE DISODIUM; .ALPHA.-TOCOPHEROL ACETATE

SANITIZING wipes 4 health

Active ingredient

Benzalkonium Chloride 0.13%

Purpose

Antiseptic

Uses

• For handwashing to decrease bacteria on the skin.

• After changing diapers. • After assisting ill persons.

• Before contact with a person under medical care or treatment.

• Recommended for repeat use.

Warnings

For external use only.

Do not use in the eyes.

When using this product do not get into eyes. If contact occurs, rinse thoroughly with water.

Stop use and ask a doctor if irritation and redness develop. If condition persists for more than 72 hours consult a doctor.

Keep out of reach of children. If swallowed, get medical help or contact a Poison Control Center right away.

Directions

• Wet hands thoroughly with product and allow to dry.

• Children under six years of age should be supervised when using this product.

Other information

• Store in a cool, dry place.

Inactive ingredients

Water, Aloe Barbadensis Leaf Juice, Polysorbate 20, Glycerin, Potassium Sorbate, Fragrance, Citric Acid, Disodium EDTA, Tocopheryl Acetate (Vitamin E).

Kills 99.99% of germs

• Wet wipes clean and sanitize

• Designed to use in health facilities, health clubs, schools, and wherever germs are present

CAUTION:May irritate eyes. See side panel for further precautions and first aid instructions.

Distributed by:
wipes 4 health

P.O. Box 19126 • Topeka, KS 66619
Tel: 785.862.0340 • Fax: 785.862.0347

www.clubwipesusa.com

DIRECTIONS FOR DISPENSING: Cut small "V" out of the bag. Pull the first towel from the center of the roll approximately 6 to 8 inches. Place bag in the dispenser and at the same time feed the first towel through the opening on the dispenser.

DISPOSAL: Offer empty container for recycling. If recycling is not available, discard container in trash. Discard towel in trash after use. Do not flush.

Made in China